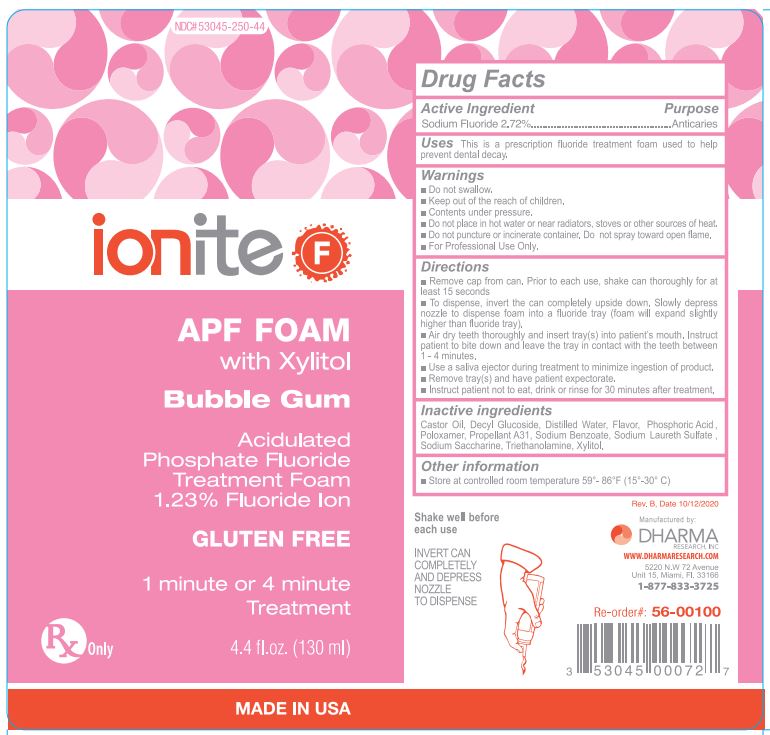 DRUG LABEL: Ionite APF
NDC: 53045-250 | Form: AEROSOL, FOAM
Manufacturer: Dharma Research, Inc.
Category: prescription | Type: HUMAN PRESCRIPTION DRUG LABEL
Date: 20201027

ACTIVE INGREDIENTS: SODIUM FLUORIDE 1.5498 g/126 g
INACTIVE INGREDIENTS: CASTOR OIL; DECYL GLUCOSIDE; WATER; HYDROFLUORIC ACID; PHOSPHORIC ACID; SODIUM BENZOATE; SODIUM LAURETH SULFATE; SACCHARIN SODIUM; XYLITOL; POLOXAMER 407; TROLAMINE

INACTIVE INGREDIENT

Castor Oil, Decyl Glucoside, Distilled Water, Flavor, Hydrofluoric Acid, Phosphoric Acid, Poloxamer, Propellant A31, Sodium Benzoate, Sodium Laureth Sulface, Sodium Saccharne, Triethanolamine, Xylitol

WARNINGS AND PRECAUTIONS

- Do not swallow.
- Keep out of reach of children.
- Contents under pressure.
- Do not place in hot water or near radiators, stoves or other sources of heat.
- Do not puncture or incinerate container. Do not spray towards open flames.
- For professional use only.

INSTRUCTIONS FOR USE

- Remove cap from can. Prior to each use, shake can thoroughly for at least 15 seconds.
- To dispense,invert the can completely upside down. Slowly depress nozzle to dispense foam into a fluoride tray (foam will expand slightly higher than fluoride tray).
- Air dry teeth thoroughly and inset tray(s) into patient's mouth. Instruct patient to bite down and leave the tray in contact with the teeth between 1 - 4 minutes.
- Use a saliva ejector during treatment to minimize ingestion of product.
- Remove the tray(s) and have patient expectorate.
- Instruct patient not to eat, drink or rinse for 30 minutes after treatment.

STORAGE AND HANDLING

Store at a controlled room temperature 59o-86oF (15o-30oC)